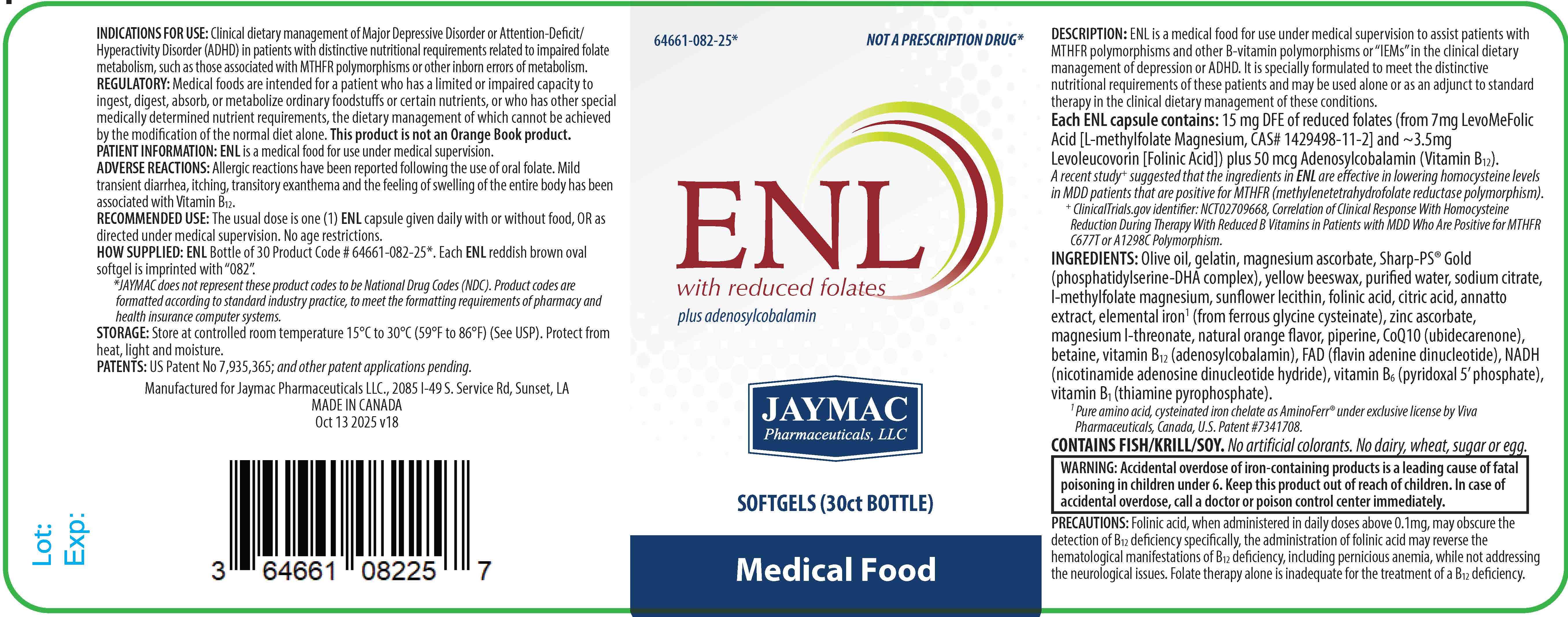 DRUG LABEL: ENL
NDC: 64661-082 | Form: CAPSULE, LIQUID FILLED
Manufacturer: Jaymac Pharma
Category: other | Type: MEDICAL FOOD
Date: 20251014

ACTIVE INGREDIENTS: LEUCOVORIN 3.5 mg/1 1; LEVOMEFOLATE MAGNESIUM 7 mg/1 1; FERROUS CYSTEINE GLYCINATE 13.6 mg/1 1; 1,2-DOCOSAHEXANOYL-SN-GLYCERO-3-PHOSPHOSERINE CALCIUM 6.4 mg/1 1; 1,2-ICOSAPENTOYL-SN-GLYCERO-3-PHOSPHOSERINE CALCIUM 800 ug/1 1; PHOSPHATIDYL SERINE 12 mg/1 1; PYRIDOXAL PHOSPHATE ANHYDROUS 25 ug/1 1; FLAVIN ADENINE DINUCLEOTIDE 25 ug/1 1; NADH 25 ug/1 1; COBAMAMIDE 50 ug/1 1; COCARBOXYLASE 25 ug/1 1; MAGNESIUM ASCORBATE 24 mg/1 1; ZINC ASCORBATE 1 mg/1 1; MAGNESIUM L-THREONATE 1 mg/1 1; BETAINE 500 ug/1 1; CITRIC ACID MONOHYDRATE 1.83 mg/1 1; SODIUM CITRATE 3.67 mg/1 1
INACTIVE INGREDIENTS: ANNATTO; GELATIN; GLYCERIN; LECITHIN, SUNFLOWER; OLIVE OIL; PIPERINE; WATER; UBIDECARENONE; YELLOW WAX

ENLTM plus adenosylcobalamin

ENLTM

with reduced folates and adenosylcobalamin

[50 mg CBl] [15 mg DFE Folate]

JAYMAC Pharmaceuticals, LLC

Softgels (30ct bottle)

Medical Food For Therapeutic Use

Description

ENLTMis a medical food for use under medical supervision to assist patients with MTHFR polymorphisms and other B-vitamin polymorphisms or “IEMs” in the clinical dietary management of depression or ADHD. It is specially formulated to meet the distinctive nutritional requirements of these patients and may be used alone or as an adjunct to standard therapy in the clinical dietary management of these conditions.

Each ENLTM capsule contains 15 mg DFE of reduced folates (from 7mg LevoMeFolic Acid [L-methylfolate Magnesium, CAS# 1429498-11-2] and ~3.5mg Levoleucovorin [Folinic Acid]) plus Adenosylcobalamin.

A recent study^+ suggested that EnLyte® was effective in lowering homocysteine levels in patients that are positive for MTHFR (methylenetetrahydrofolate reductase polymorphism).

^+ClinicalTrials.gov identifier: NCT02709668, Correlation of Clinical Response With Homocysteine Reduction During Therapy With Reduced B Vitamins in Patients with MDD Who Are Posititive for MTHFR C677T or A1298C Polymorphism.

INACTIVE INGREDIENT

INGREDIENTS: Olive oil, gelatin, magnesium ascorbate, Sharp-PS® Gold (phosphatidylserine-DHA complex), yellow beeswax, purified water, sodium citrate, l-methylfolate magnesium, sunflower lecithin, folinic acid, citric acid, annatto extract, elemental iron^1 (from ferrous glycine cysteinate), zinc ascorbate, magnesium l-threonate, natural orange flavor, piperine, CoQ10 (ubidecarenone), betaine, vitamin B12 (adenosylcobalamin), FAD (flavin adenine dinucleotide), NADH (nicotinamide adenosine dinucleotide hydride), vitamin B6 (pyridoxal 5’ phosphate), vitamin B1 (thiamine pyrophosphate).

^1 Pure amino acid, cysteinated iron chelate as AminoFerr® under exclusive license by Viva Pharmaceuticals, Canada, U.S. Patent #7341708.

CONTAINS FISH/KRILL/SOY. No artificial colorants. No dairy, wheat, sugar or egg.

INDICATION FOR USE:

Clinical dietary management of Major Depressive Disorder or Attention-Deficit/Hyperactivity Disorder (ADHD) in patients with distinctive nutritional requirements related to impaired folate metabolism, such as those associated with MTHFR polymorphisms or other inborn errors of metabolism.

ADVERSE REACTIONS:

Allergic reactions have been reported following the use of oral folate. Mild transient diarrhea, itching, transitory exanthema and the feeling of swelling of the entire body has been associated with Vitamin B12.

PRECAUTIONS:

Folinic acid, when administered in daily doses above 0.1 mg, may obscure the detection of B12 deficiency specifically, the administration of folinic acid may reverse the hematological manifestations of B12 deficiency, including pernicious anemia, while not addressing the neurological issues. Folate therapy alone is inadequate for the treatment of a B12 deficiency.

RECOMMENDED USE:

The usual dose is one (1) ENL capsule given daily with or without food, or as directed under medical supervision. No age restrictions.

You may report side effects by calling 337.662-5962.

KEEP THIS OUT OF THE REACH OF CHILDREN.

Do not exceed the recommended dose.

HOW SUPPLIED:

ENL Bottle of 30 Product Code # 64661-082-25*. Each ENL reddish brown oval softgel is imprinted with “082”.

*JAYMAC does not represent these product codes to be National Drug Codes (NDC). Product codes are formatted according to standard industry practice, to meet the formatting requirements of pharmacy and health insurance computer systems.

STORAGE:

Store at controlled room temperature 15°C to 30°C (59°F to 86°F) (See USP). Protect from heat, light and moisture.

(Tamper Evident: Do not use if seal is broken or missing.)

JAYMAC Pharmaceuticals, LLC, 2085 I-49 S. Service Rd, Sunset, LA 70584

MANUFACTURED AND/OR PACKAGED IN USA/CANADA

Rev April 10, 2024 (V17)